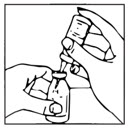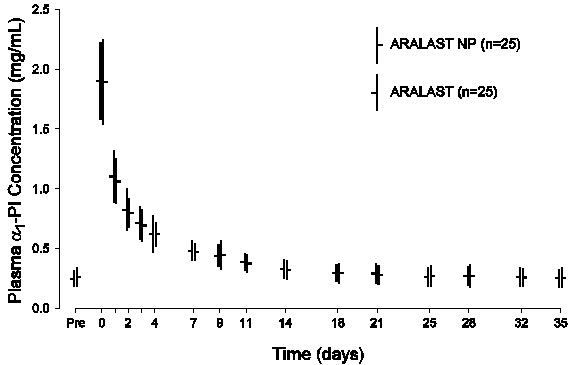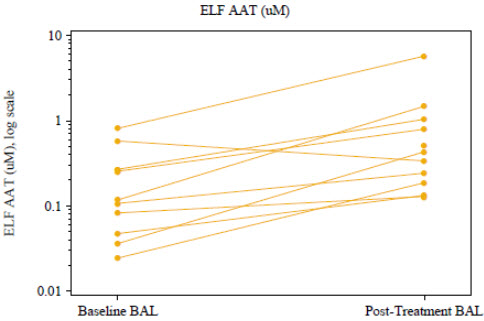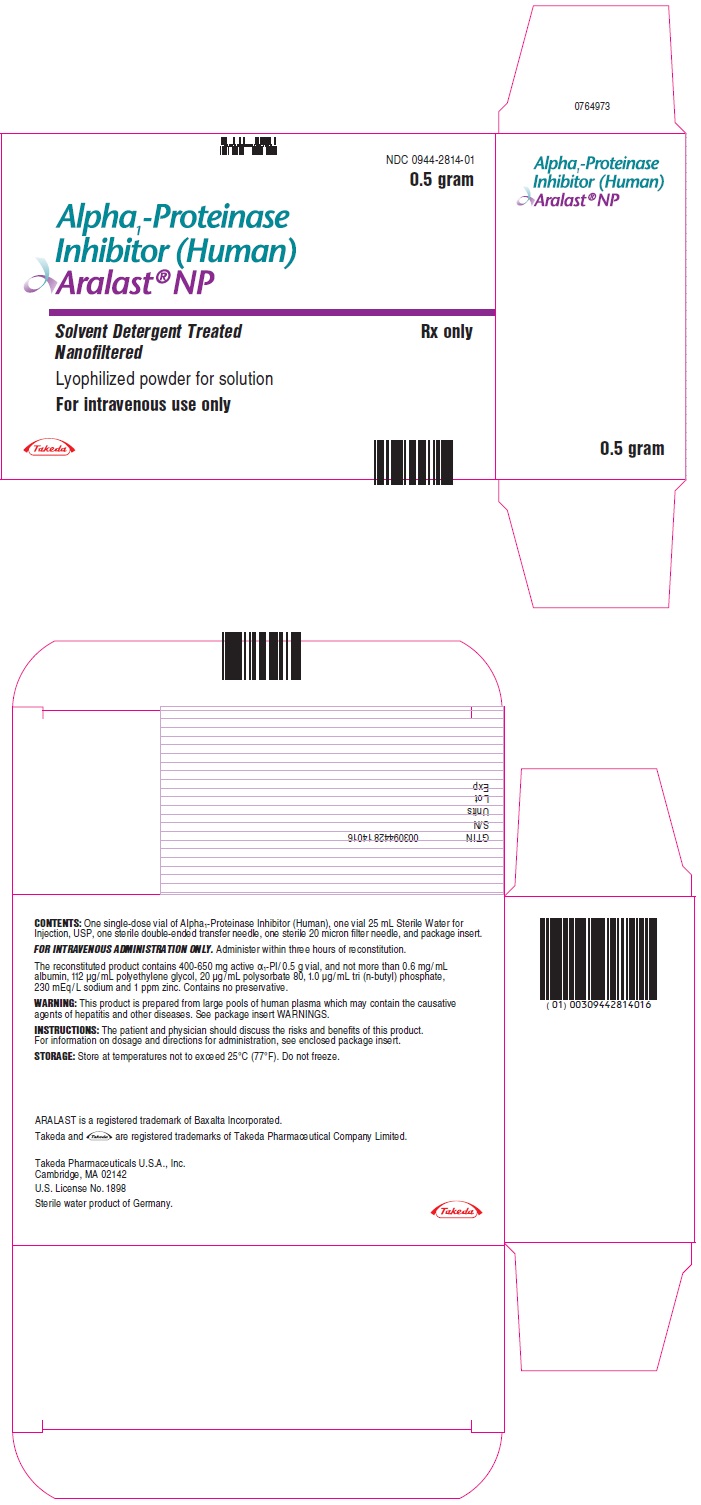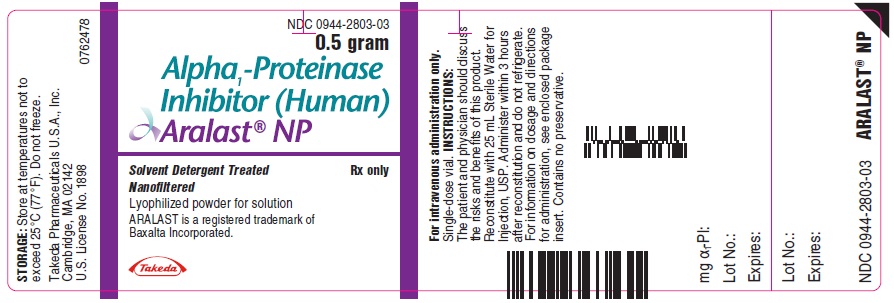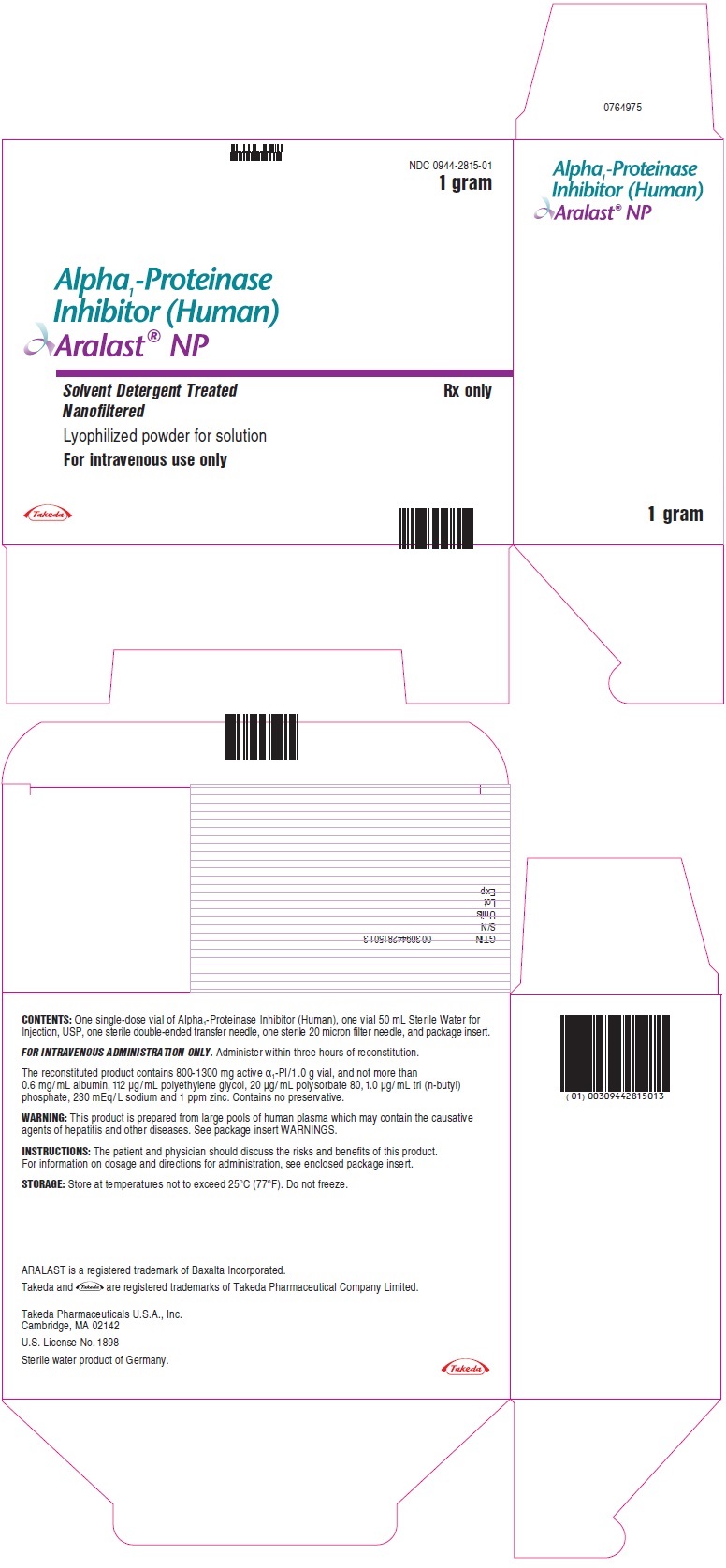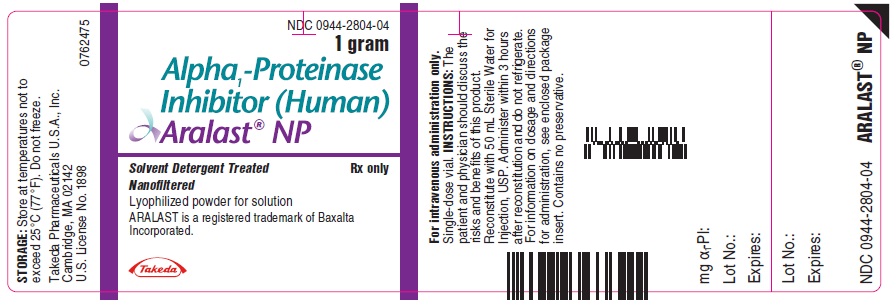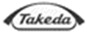 DRUG LABEL: Aralast
NDC: 0944-2814 | Form: KIT | Route: INTRAVENOUS
Manufacturer: Takeda Pharmaceuticals America, Inc.
Category: other | Type: PLASMA DERIVATIVE
Date: 20251125

ACTIVE INGREDIENTS: .ALPHA.1-PROTEINASE INHIBITOR HUMAN 16 mg/1 mL
INACTIVE INGREDIENTS: ALBUMIN HUMAN; POLYETHYLENE GLYCOL 3350; POLYSORBATE 80; SODIUM CHLORIDE; TRI-N-BUTYL PHOSPHATE; ZINC; WATER 25 mL/25 mL

HIGHLIGHTS OF PRESCRIBING INFORMATION

These highlights do not include all the information needed to use ARALAST NP safely and effectively. See full prescribing information for ARALAST NP.
ARALAST® NP (Alpha1-Proteinase Inhibitor (Human))
For Intravenous Use. Lyophilized Powder for Solution for Injection
Initial U.S. Approval: 2002

1 INDICATIONS AND USAGE

ARALAST NP is an Alpha1-Proteinase Inhibitor (Human) (Alpha1-PI) indicated for chronic augmentation therapy in adults with clinically evident emphysema due to severe congenital deficiency of Alpha1-PI (alpha1-antitrypsin deficiency). ARALAST NP increases antigenic and functional (anti-neutrophil elastase capacity, ANEC) serum levels and antigenic lung epithelial lining fluid levels of Alpha1-PI. (1)

The effect of augmentation therapy with any Alpha1-PI, including ARALAST NP, on pulmonary exacerbations and on the progression of emphysema in alpha1-antitrypsin deficiency has not been conclusively demonstrated in randomized, controlled clinical trials. (1)

Clinical data demonstrating the long-term effects of chronic augmentation and maintenance therapy of individuals with ARALAST NP or ARALAST are not available. (1)

ARALAST NP is not indicated as therapy for lung disease in patients in whom severe Alpha1-PI deficiency has not been established. (1)

2 DOSAGE AND ADMINISTRATION

For Intravenous Use Only

- Recommended dosage is 60 mg/kg body weight administered once weekly by intravenous infusion. (2.1)
- Administer at a rate not to exceed 0.2 mL/kg body weight/minute, and as determined by the response and comfort of the patient. (2.3)

3 DOSAGE FORMS AND STRENGTHS

Available as a lyophilized powder in single dose vials containing 0.5 gram or 1 gram of functional Alpha1-PI. (3)

4 CONTRAINDICATIONS

Immunoglobulin A (IgA) deficient patients with antibodies against IgA. (4)

5 WARNINGS AND PRECAUTIONS

- Severe hypersensitivity and anaphylactic reactions may occur in IgA deficient patients with antibodies against IgA. (5.1)
- May carry a risk of transmitting infectious agents such as viruses, the variant Creutzfeldt-Jakob disease (vCJD) and theoretically, the Creutzfeldt-Jakob disease (CJD) agent, despite manufacturing steps designed to minimize the risk of viral transmission. (5.2)

6 ADVERSE REACTIONS

Most common adverse reaction occurring in ≥5% of infusions in clinical studies were headache, musculoskeletal discomfort, vessel puncture site bruise, nausea, and rhinorrhea. (6.1)

To report SUSPECTED ADVERSE REACTIONS, contact Takeda Pharmaceuticals U.S.A., Inc. at 1-877-TAKEDA-7 (1-877-825-3327) or FDA at 1-800-FDA-1088 or www.fda.gov/medwatch.

FULL PRESCRIBING INFORMATION

1 INDICATIONS AND USAGE

ARALAST NP is an Alpha1-Proteinase Inhibitor (Alpha1-PI) indicated for chronic augmentation therapy in adults with clinically evident emphysema due to severe congenital deficiency of Alpha1-PI (alpha1-antitrypsin deficiency). ARALAST NP increases antigenic and functional (anti-neutrophil elastase capacity, ANEC) serum levels and antigenic lung epithelial lining fluid levels of Alpha1-PI.

The effect of augmentation therapy with any Alpha1-PI, including ARALAST NP, on pulmonary exacerbations and on the progression of emphysema in alpha1-antitrypsin deficiency has not been conclusively demonstrated in randomized, controlled clinical trials.

Clinical data demonstrating the long-term effects of chronic augmentation and maintenance therapy with ARALAST NP or ARALAST are not available.

ARALAST NP is not indicated as therapy for lung disease in patients in whom severe congenital Alpha1-PI deficiency has not been established.

2 DOSAGE AND ADMINISTRATION

For Intravenous Use Only

2.1 Dosage

- Dose ranging studies using efficacy endpoints have not been performed.
- Administer 60 mg/kg body weight of ARALAST NP once weekly by intravenous infusion.

2.2 Reconstitution

1. Use aseptic technique.
2. Allow ARALAST NP and diluent to reach room temperature before reconstitution.
3. Remove caps from the diluent and product vials.
4. Swab the exposed stopper surfaces with alcohol.
5. Remove cover from one end of the double-ended transfer needle. Insert the exposed end of the needle through the center of the stopper in the diluent vial.
6. Remove plastic cap from the other end of the double-ended transfer needle now seated in the stopper of the diluent vial. To reduce any foaming, invert the vial of diluent and insert the exposed end of the needle through the center of the stopper in the product vial at an angle, making certain that the diluent vial is always above the product vial. The angle of insertion directs the flow of diluent against the side of the product vial. Refer to Figure 1 below. The vacuum in the vial is sufficient to allow transfer of all of the diluent.
  Figure 1
7. Disconnect the two vials by removing the diluent vial from the transfer needle. This allows any remaining low pressure in the product vial to equalize. Next, remove the double-ended transfer needle from the product vial and discard the needle into the appropriate safety container.
8. Let the vial stand until most of the contents is in solution, then GENTLY swirl until the powder is completely dissolved. Reconstitution requires no more than five minutes for a 0.5 gram vial and no more than 10 minutes for a 1 gram vial.
  Note: Do not shake the content of the vial. Do not invert the vial until ready to withdraw content.
9. Reconstituted product is a colorless or slightly yellow to yellow-green solution.
10. A few small visible particles may occasionally remain in the reconstituted product. These will be removed by the sterile 20 micron filter needle supplied with the product.
11. Place the product vial on a stable flat surface.
12. Open the blister pack of the 20 micron filter needle.
13. Twist to remove the protective cap from the Luer adapter of the filter needle.
14. Attach a single-use syringe (not provided) to the Luer adapter of the filter needle.
15. Remove the protective cap from the filter needle and draw back plunger of the syringe to admit air into syringe. Insert the filter needle through the center of the stopper in product vial.
16. Push the plunger to admit air in the product vial.
17. Invert the system (product vial with syringe attached) so that product vial is on top.
18. Withdraw the reconstituted product into the syringe.
19. Remove the syringe from the filter needle and product vial. Remove filter needle from product vial and discard the needle into the appropriate sharps container.

2.3 Administration

For intravenous infusion

1. Product from multiple vials may be pooled to achieve the calculated dose [see Dosage and Administration (2.1)].
2. Several vials may be pooled using a separate needle (not provided) into an empty, sterile intravenous solution container using aseptic technique.
3. Inspect the filtered reconstituted product visually for particulate matter and discoloration prior to administration. Administer ARALAST NP within three hours after reconstitution to reduce the risk of harmful microbial growth. Discard any unused contents.
4. Administer ARALAST NP alone, without mixing with other agents or diluting solutions.

Infusion Rate

- Administer ARALAST NP at a rate not to exceed 0.2 mL per kg body weight per minute, and as determined by the response and comfort of the patient.
- Reduce the infusion rate or halt the infusion if adverse reactions occur. Resume the infusion at a rate tolerated by the patient after symptoms subside.

3 DOSAGE FORMS AND STRENGTHS

ARALAST NP is available as a lyophilized powder in single dose vials containing 0.5 gram or 1 gram of functional Alpha1-PI.

4 CONTRAINDICATIONS

ARALAST NP is contraindicated in immunoglobulin A (IgA) deficient patients with antibodies against IgA, due to the risk of severe hypersensitivity.

5 WARNINGS AND PRECAUTIONS

5.1 Hypersensitivity Reactions

ARALAST NP may contain trace amounts of IgA. Patients with known antibodies to IgA, which can be present in patients with selective or severe IgA deficiency, have a greater risk of developing severe hypersensitivity and anaphylactic reactions. Closely follow the recommended infusion rate [see Dosage and Administration (2.3)]. Monitor vital signs continuously and observe the patient carefully throughout the infusion. Discontinue the infusion if hypersensitivity symptoms occur and administer appropriate emergency treatment. Have epinephrine and other appropriate supportive therapy available for the treatment of any acute anaphylactic or anaphylactoid reaction.

5.2 Transmission of Infectious Agents

Because this product is made from human plasma, it may carry a risk of transmitting infectious agents, such as viruses, the variant Creutzfeldt-Jakob disease (vCJD) and theoretically, the Creutzfeldt-Jakob disease (CJD) agent. This also applies to unknown or emerging viruses and other pathogens. The risk of transmitting an infectious agent has been minimized by screening plasma donors for prior exposure to certain viruses, by testing for the presence of certain virus infections and by inactivating and removing certain viruses during the manufacturing process. Despite these measures, such products may still potentially transmit human pathogenic agents.

No seroconversions for hepatitis B or C (HBV or HCV) or human immunodeficiency virus (HIV) or any other known infectious agent were reported with the use of ARALAST NP during clinical studies.

All infections thought by a physician to possibly have been transmitted by this product should be reported by the physician or other healthcare provider to Takeda Pharmaceuticals U.S.A., Inc., at 1-877-TAKEDA-7 (1-877-825-3327) (in the U.S.).

6 ADVERSE REACTIONS

Hypersensitivity reactions have been reported in patients following administration of ARALAST/ARALAST NP [see Warnings and Precautions (5.1)].

No serious adverse reactions related to the use of ARALAST NP were reported in clinical trials. The most common adverse reactions occurring in ≥5% of infusions in clinical trials were headache, musculoskeletal discomfort, vessel puncture site bruise, nausea, and rhinorrhea.

6.1 Clinical Trials Experience

Because clinical trials are conducted under widely varying conditions, adverse reaction rates observed in the clinical trials of a drug cannot be directly compared to rates in the clinical trials of another drug and may not reflect the rates observed in clinical practice.

The safety of ARALAST NP was evaluated in a total of 38 subjects with severe congenital Alpha1-PI deficiency (pre-augmentation therapy serum levels of Alpha1-PI of less than 11 microM) in two clinical trials. The crossover trial was a multicenter, randomized, double-blind, single-dose pharmacokinetic (PK) comparability trial conducted in 25 subjects with severe congenital Alpha1-PI deficiency to evaluate the pharmacokinetics of ARALAST NP (test drug, 60 mg/kg body weight) as compared to ARALAST (reference drug, 60 mg/kg body weight), each infused at a rate of 0.2 mL/kg body weight/minute. The BAL trial was a multicenter, open-label, non-randomized trial in 13 subjects with severe congenital Alpha1-PI deficiency to determine the safety and effects of weekly augmentation therapy with ARALAST NP (60 mg/kg body weight/week) administered at a rate of 0.2 mL/kg body weight/minute in elevating Alpha1-PI levels in serum and epithelial lining fluid (ELF).

In both trials, there were no deaths and no serious adverse reactions associated with ARALAST NP or ARALAST administration. None of the subjects withdrew from the trial due to an adverse reaction. There was no reduction in infusion rate at 0.2 mL/kg body weight/min or infusion discontinuation/interruption due to an adverse reaction, except for one subject in the crossover trial who experienced pain at infusion site during ARALAST administration.

Table 1 summarizes the number of subjects, the total number of infusions, and the rate of adverse reactions (ARs) associated with ARALAST NP or ARALAST treatment for each clinical trial.

Table 1: Number of Subjects/Infusions/Adverse Reactions (ARs) [An adverse reaction (AR) is any adverse event which met any of the following criteria: (a) an adverse event that began during infusion or within 72 hours following the end of product infusion, or (b) an adverse event considered by the investigator to be at least possibly related to product administration, or (c) an adverse event for which causality assessment was missing or indeterminate.] Occurring during ARALAST NP or ARALAST Treatment
 | Crossover Trial | Crossover Trial | BAL Trial
 | ARALAST NP | ARALAST | ARALAST NP
No. of subjects treated | 25 | 25 | 13
No. of infusions | 25 | 25 | 104
No. (%) of subjects with serious ARs | 0 (0%) | 0 (0%) | 0 (0%)
No. of serious ARs | 0 | 0 | 0
No. (%) of subjects with non-serious ARs | 12 (48%) | 13 (52%) | 4 (31%)
No. of non-serious ARs | 26 | 21 | 14
No. (%) of Mild [A mild reaction was defined as a transient discomfort that does not interfere in a significant manner with the subject's normal functioning level, or an event that resolves spontaneously or may require minimal therapeutic intervention] ARs | 21 (81%) | 16 (76%) | 8 (57%)
No. (%) of Moderate [A moderate reaction was defined as an event that is considered related to study product and that produces limited impairment of function and can require therapeutic intervention, or that produces no sequelae] ARs | 5 (19%) | 5 (24%) | 5 (36%)
No. (%) of Severe [A severe reaction was defined as an event that is considered related to study product and that results in a marked impairment of function and can lead to temporary inability to resume usual life pattern, or that produces sequelae which requires prolonged therapeutic intervention] ARs | 0 (0%) | 0 (0%) | 1 (7%)

The most common ARs (defined as adverse reactions occurring in ≥5% of infusions) in each clinical trial are shown in Table 2.

Table 2: Adverse Reactions (ARs) [An adverse reaction (AR) is any adverse event which met any of the following criteria: (a) an adverse event that began during infusion or within 72 hours following the end of product infusion, or (b) an adverse event considered by the investigator to be at least possibly related to product administration, or (c) an adverse event for which causality assessment was missing or indeterminate.] Occurring in ≥5% of Infusions
 | Crossover Trial (Number of Subjects = 25; Number of infusions per product = 25) | Crossover Trial (Number of Subjects = 25; Number of infusions per product = 25) | BAL Trial (Number of Subjects = 13; Number of infusions = 104)
Reaction | ARALAST NP N (%) [Expressed as number of events (N) divided by total number of infusions, then multiplied by 100.] | ARALAST N (%) | ARALAST NP N (%)
Headache | 4 (16%) | 3 (12%) | 0 (0%)
Musculoskeletal discomfort | 4 (16%) | 2 (8%) | 0 (0%)
Vessel puncture site bruise | 2 (8%) | 4 (16%) | 0 (0%)
Lethargy | 0 (0%) | 2 (8%) | 0 (0%)
Nausea | 2 (8%) | 2 (8%) | 0 (0%)
Rhinorrhea | 1 (4%) | 0 (0%) | 6 (6%)

ARALAST versus PROLASTIN Trial

ARALAST was evaluated for up to 96 weeks in 27 subjects with a congenital deficiency of Alpha1-PI and clinically evident emphysema. During the initial 10 weeks of the trial, subjects were randomized to receive either ARALAST or a commercially available preparation of Alpha1-PI (PROLASTIN).

During the entire period of administration of ARALAST, the most common adverse reactions occurring at a rate of >0.5% of infusions included pharyngitis (1.2%), headache (0.8%), and cough increased (0.5%). Adverse reactions that occurred at rates <0.5% included somnolence, rash, tinnitus, back pain, chest pain, peripheral edema, dizziness, insomnia, bronchitis, abdomen enlarged, abdominal pain, allergic reaction, pruritus, chills, fever, vasodilation, nausea, hypertonia, hypesthesia, nervousness, asthma, dyspnea, lung disorder, abnormal vision, conjunctivitis, and dysmenorrhea.

Twenty-six (26) of 27 (96.3%) subjects experienced a total of 94 upper and lower respiratory-tract infections during the 96-week trial (median: 3.0; range: 1 to 8; mean ± SD: 3.6 ± 2.3 infections). Twenty-eight (29.8%) of the respiratory infections occurred in 19 (70.4%) subjects during the first 24 weeks of the 96-week trial suggesting that the risk of infection did not change with time on ARALAST. In a post-hoc analysis, subjects experienced a range of 0 to 8 exacerbations of COPD over the 96-week trial with a median of less than one exacerbation per year (median: 0.61; mean ± SD: 0.83 ± 0.87 exacerbations per year).

Treatment-emergent elevations (> two times the upper limit of normal) in aminotransferases (ALT or AST), up to 3.7 times the upper limit of normal, were noted in 3 of 27 (11.1%) subjects. Elevations were transient lasting three months or less. No subject developed any evidence of viral hepatitis or hepatitis seroconversion while being treated with ARALAST, including 13 evaluable subjects who were not vaccinated against hepatitis B.

No clinically relevant alterations in blood pressure, heart rate, respiratory rate, or body temperature occurred during infusion of ARALAST. Mean hematology and routine clinical chemistry (other than ALT) laboratory parameters were little changed over the duration of the trial, with individual variations not clinically meaningful.

There were no serious adverse reactions or seroconversions reported for the ARALAST group during the 96 week trial period. No subject developed antibodies to Alpha1-PI.

Immunogenicity

- The detection of antibody formation is highly dependent on the sensitivity and specificity of the assay. Additionally, the observed incidence of antibody (including neutralizing antibody) positivity in an assay may be influenced by several factors including assay methodology, sample handling, timing of sample collection, concomitant medications, and underlying disease. For these reasons, comparison of the incidence of antibodies to ARALAST NP with the incidence of antibodies to other products may be misleading.
- Immunogenicity of ARALAST NP was evaluated in the BAL trial. None of the treated subjects developed antibodies against ARALAST NP.

6.2 Postmarketing Experience

The following adverse reactions have been identified during post-approval use of ARALAST NP. Because these reactions are reported voluntarily from a population of uncertain size, it is not always possible to reliably estimate their frequency or establish a causal relationship to drug exposure.

Vascular Disorders: Flushing

Gastrointestinal Disorders: Vomiting, Diarrhea

Skin and Subcutaneous Tissue Disorders: Urticaria

Musculoskeletal and Connective Tissue Disorders: Myalgia

General and Administration Site Conditions: Injection site reaction, Fatigue, Malaise, Asthenia, Feeling abnormal

8 USE IN SPECIFIC POPULATIONS

8.1 Pregnancy

Risk Summary

There are no data with ARALAST NP use in pregnant women to inform a drug-associated risk. Animal reproduction studies have not been conducted with ARALAST NP. It is also not known whether ARALAST NP can cause fetal harm when administered to pregnant women or can affect reproductive capacity.

In the U.S. general population, the estimated background risk of major birth defect and miscarriage in clinically recognized pregnancies is 2-4% and 15-20%, respectively.

8.2 Lactation

Risk Summary

There is no information regarding the presence of ARALAST NP in human milk, the effect on the breastfed infant, or the effects on milk production.

The developmental and health benefits of breastfeeding should be considered along with the mother's clinical need for ARALAST NP and any potential adverse effects on the breastfed infant from ARALAST NP or from the underlying maternal condition.

8.4 Pediatric Use

Safety and effectiveness in pediatric patients have not been established.

8.5 Geriatric Use

Clinical studies of ARALAST NP did not include sufficient numbers of subjects aged 65 and over to determine whether they respond differently from younger subjects. As for all patients, dosing for geriatric patients should be appropriate to their overall situation. Safety and effectiveness in patients over age 65 years of age have not been established.

11 DESCRIPTION

ARALAST NP contains approximately 2% Alpha1-PI with truncated C-terminal lysine (removal of Lys394), whereas ARALAST contains approximately 67% Alpha1-PI with the C-terminal lysine truncation.^8 No known data suggest influence of these structural modifications on the functional activity and immunogenicity of Alpha1-PI.^9

ARALAST NP is a sterile, lyophilized preparation of purified human alpha1-proteinase inhibitor (Alpha1-PI), also known as alpha1-antitrypsin (AAT).^1 ARALAST NP is a similar product to ARALAST, containing the same active components of plasma Alpha1-PI with identical formulations.

ARALAST NP is prepared from large pools of human plasma by using the cold ethanol fractionation process, followed by purification steps including polyethylene glycol and zinc chloride precipitations and ion exchange chromatography.

To reduce the risk of viral transmission, the manufacturing process includes treatment with a solvent detergent (S/D) mixture [tri-n-butyl phosphate and polysorbate 80] to inactivate enveloped viral agents such as human immunodeficiency virus (HIV), hepatitis B (HBV), and hepatitis C (HCV). In addition, a nanofiltration step is incorporated into the manufacturing process to reduce the risk of transmission of enveloped and non-enveloped viral agents. Based on in vitro studies, the process used to produce ARALAST NP has been shown to inactivate and/or partition various viruses as shown in Table 3 below.

Table 3: Virus Log Reduction in ARALAST NP Manufacturing Process
Processing Step | Virus Log Reduction Factors HIV-1 | Virus Log Reduction Factors BVDV | Virus Log Reduction Factors PRV | Virus Log Reduction Factors HAV | Virus Log Reduction Factors MMV
Cold ethanol fractionation | 4.6 | 1.4 | 2.1 | 1.4 | ≤1.0 [Reduction factors ≤1 are not used for calculation of the overall reduction factor.]
Solvent Detergent-treatment | >5.8 | >6.0 | >5.5 | N/A | N/A
15 N nanofiltration | >5.3 | >6.0 | >5.6 | >5.1 | 4.9
Overall reduction factor | >15.7 | >13.4 | >13.2 | >6.5 | 4.9
N/A – Not applicable; study did not test for virus indicated.
HIV–1: Human Immunodeficiency Virus-1; BVDV: Bovine Viral Diarrhea Virus, model for Hepatitis C Virus and other lipid enveloped RNA viruses; PRV: Pseudorabies Virus, model for lipid-enveloped DNA viruses, to which Hepatitis B also belongs; HAV: Hepatitis A Virus; MMV: Mice Minute Virus, model for small non-lipid-enveloped DNA viruses

The unreconstituted, lyophilized cake should be white or off-white to slightly yellow-green or yellow in color. When reconstituted as directed, the concentration of functionally active Alpha1-PI is 16.0 – 26.0 mg/mL and the specific activity is ≥0.55 mg active Alpha1-PI/mg total protein. The composition of the reconstituted product is as follows:

Component | Quantity/mL
Elastase Inhibitory Activity | 400 – 650 mg Active Alpha1-PI/0.5 g vial [Reconstitution volume: 25 mL/0.5 g vial] 800 – 1300 mg Active Alpha1-PI/1 g vial [Reconstitution volume: 50 mL/1 g vial]
Albumin | ≤0.6 mg/mL
Polyethylene Glycol | ≤112 mcg/mL
Polysorbate 80 | ≤20 mcg/mL
Sodium | ≤230 micromol/mL
Tri-n-butyl Phosphate | ≤1 mcg/mL
Zinc | ≤1.0 mg/L

Each vial of ARALAST NP has the functional activity, as determined by inhibition of porcine pancreatic elastase, stated on the label. The formulation contains no preservative. The pH of the solution ranges from 7.2 to 7.8. Product must only be administered intravenously.

12 CLINICAL PHARMACOLOGY

12.1 Mechanism of Action

ARALAST NP administration is intended to inhibit serine proteases such as neutrophil elastase (NE), which is capable of degrading protein components of the alveolar walls and which is chronically present in the lung.

Alpha1-PI deficiency is an autosomal, co-dominant, hereditary disorder characterized by low serum and lung levels of Alpha1-PI.^1,2,4,5 Severe forms of the deficiency are frequently associated with slowly progressive, moderate-to-severe panacinar emphysema that most often manifests in the third to fourth decades of life.^1,2,3,5,6 However, an unknown percentage of individuals with severe Alpha1-PI deficiency are not diagnosed with or may never develop clinically evident emphysema during their lifetimes. Individuals with Alpha1-PI deficiency have little protection against NE released by neutrophils in their lower respiratory tract, resulting in a protease:protease inhibitor imbalance in the lung.^2,7 This imbalance allows relatively unopposed destruction of the connective tissue framework of the lung parenchyma.^7

There are a large number of phenotypic variants of this disorder.^1,2,3 Individuals with the PiZZ variant typically have serum Alpha1-PI levels less than 35% of the average normal level.^1,4 Individuals with the Pi(null)(null) variant have undetectable Alpha1-PI protein in their serum.^1,2 Individuals with these low serum Alpha1-PI levels, i.e., less than 11 microM, have an increased risk of developing emphysema over their lifetimes. In addition, PiSZ individuals, whose serum Alpha1-PI levels range from approximately 9 to 23 microM,^10 are considered to have moderately increased risk for developing emphysema, regardless of whether their serum Alpha1-PI levels are above or below 11 microM. The risk of accelerated development and progression of emphysema in individuals with severe Alpha1-PI deficiency is higher in smokers than in ex-smokers or non-smokers.^2

Not all individuals with severe genetic variants of Alpha1-PI deficiency have emphysema. Augmentation therapy with Alpha1-Proteinase Inhibitor (Human) is indicated only in patients with severe congenital Alpha1-PI deficiency who have clinically evident emphysema.

Augmenting the levels of functional Alpha1-proteinase inhibitor by intravenous infusion is an approach to therapy for patients with Alpha1-PI deficiency. However, the efficacy of augmentation therapy in affecting the progression of emphysema has not been demonstrated in randomized, controlled clinical trials. The intended theoretical goal is to provide protection to the lower respiratory tract by correcting the imbalance between neutrophil elastase and protease inhibitors. Whether augmentation therapy with ARALAST NP actually protects the lower respiratory tract from progressive emphysematous changes has not been evaluated. Although the maintenance of blood serum levels of Alpha1-PI (antigenically measured) above 11 microM has been historically postulated to provide therapeutically relevant anti-neutrophil elastase protection, this has not been proven. Individuals with severe Alpha1-PI deficiency have been shown to have increased neutrophil and neutrophil elastase concentrations in lung epithelial lining fluid compared to normal PiMM individuals, and some PiSZ individuals with Alpha1-PI above 11 microM have emphysema attributed to Alpha1-PI deficiency. These observations underscore the uncertainty regarding the appropriate therapeutic target serum level of Alpha1-PI during augmentation therapy. The clinical benefit of increased blood levels of Alpha1-PI at the recommended dose has not been established.

The clinical efficacy of ARALAST NP in influencing the course of pulmonary emphysema or the frequency, duration, or severity of pulmonary exacerbations has not been demonstrated in randomized, controlled clinical trials.

12.2 Pharmacodynamics

Chronic augmentation therapy with a weekly dose of ARALAST NP at 60 mg/kg body weight to patients with Alpha1-PI deficiency increases the level of the deficient protein in plasma and in the epithelial lining fluid (ELF) as determined by antigenic assay. Normal individuals have plasma levels of Alpha1-PI greater than 20 microM. The clinical benefit of increased blood and ELF levels of Alpha1-PI at the recommended dose has not been demonstrated in adequately powered, randomized, double-blind, placebo-controlled trials for any Alpha1-PI product.

12.3 Pharmacokinetics

The pharmacokinetic comparability of ARALAST NP and the predecessor product ARALAST was demonstrated in a randomized, double-blind, crossover trial in 25 subjects (median age: 59 years old; range: 20 to 75 years old) with severe Alpha1-PI deficiency who received a single infusion of 60 mg/kg body weight of each product. Figure 2 depicts the mean ± standard deviation (SD) plasma Alpha1-PI concentration-time profiles measured using an enzyme-linked immunosorbent assay (ELISA). Table 4 summarizes the pharmacokinetic parameters of ARALAST NP and ARALAST.

Mean (± SD) Plasma Alpha1-PI Concentration-Time Profiles After a Single Intravenous Infusion of ARALAST NP and ARALAST (60 mg/kg) in Subjects with Congenital Alpha1-PI Deficiency

Figure 2

Table 4: Pharmacokinetic Parameters for Plasma Antigenic Alpha1-PI in 25 Subjects Following a Single 60 mg/kg Dose of ARALAST NP or ARALAST
Pharmacokinetic Parameter | ARALAST NP Mean (± SD) | ARALAST Mean (± SD)
Cmax | 1.6 (± 0.3) mg/mL | 1.7 (± 0.3) mg/mL
AUC0-35d/dose | 0.0837 (± 0.0212) day*kg/mL | 0.0897 (± 0.0204) day*kg/mL
Half-life | 4.7 (± 2.7) days | 4.8 (± 2.0) days
Cmax = Maximum increase in plasma Alpha1-PI concentration following infusion; AUC0-35d/dose = Area under the curve from time 0 to 35 days divided by dose; Half-life = terminal phase half-life determined using non-compartmental method.

The key pharmacokinetic parameter was AUC0-35d/dose. The 90% confidence interval (85.8% to 100.2%) for the geometric mean ratio of AUC0-35d/dose for ARALAST NP and ARALAST indicated that the 2 products are pharmacokinetically equivalent.

13 NONCLINICAL TOXICOLOGY

13.1 Carcinogenesis, Mutagenesis, Impairment of Fertility

Long-term studies in animals to evaluate the carcinogenic potential of ARALAST NP have not been conducted. In vitro and in vivo testing of ARALAST NP for mutagenesis or impairment of fertility was not performed.

14 CLINICAL STUDIES

A clinical trial (ARALAST versus PROLASTIN trial) was conducted to compare the predecessor product ARALAST to a commercially available preparation of Alpha1-PI (PROLASTIN) in 28 subjects with congenital Alpha1-PI deficiency and emphysema, who had not received Alpha1-PI augmentation therapy within the preceding six months.

Subjects were randomized to receive either ARALAST or PROLASTIN, 60 mg/kg intravenously per week for 10 consecutive weeks. Following their first 10 weekly infusions, the subjects who were receiving PROLASTIN were switched to ARALAST while those who already were receiving ARALAST continued to receive it. Table 5 summarizes the mean serum antigenic and functional Alpha1-PI trough levels measured prior to infusion at steady state (Weeks 8 through 11).

Table 5: Steady-State Serum Antigenic and Functional Alpha1-PI Trough Levels Following Intravenous Augmentation Therapy with ARALAST or PROLASTIN
 | ARALAST Mean ± SD (Range of means) (No. of Subjects = 13) | PROLASTIN Mean ± SD (Range of means) (No. of Subjects = 13)
Antigenic Alpha1-PI | 15.3 ± 2.5 (14.7 to 15.5) microM | 16.9 ± 2.3 (16.2 to 17.2) microM
Functional Alpha1-PI | 15.3 ± 2.4 (14.8 to 15.6) microM | 15.7 ± 2.6 (14.4 to 16.4) microM

Following weekly augmentation therapy with ARALAST or PROLASTIN, a gradual increase in peak and trough serum Alpha1-PI levels was noted, with stabilization after several weeks. The metabolic half-life of ARALAST was 5.9 days. Serum ANEC trough levels rose substantially in all subjects by Week 2, and by Week 3, serum ANEC trough levels exceeded 11 microM in the majority of subjects. With few exceptions, levels in both treatment groups remained above this level in individual subjects for the duration of the period Weeks 3 through 24. Although only five of fourteen subjects (35.7%) receiving ARALAST had BALs meeting acceptance criteria for analysis at both baseline and Week 7, a statistically significant increase in the antigenic level of Alpha1-PI in epithelial lining fluid (ELF) was observed. No statistically significant increase in the ANEC in the ELF was detected.

It was concluded that at a dose of 60 mg/kg administered intravenously once weekly, ARALAST and PROLASTIN had similar effects in maintaining target serum Alpha1-PI trough levels and increasing antigenic levels of Alpha1-PI in the ELF with maintenance augmentation therapy.

The pharmacokinetic comparability of ARALAST NP and the predecessor product ARALAST was demonstrated in a randomized, double-blind, crossover trial in 25 subjects with severe Alpha1-PI deficiency [see Clinical Pharmacology (12.3)].

Another clinical trial (BAL TRIAL) was conducted to determine the effects of open-label, weekly intravenous augmentation therapy with 60 mg/kg ARALAST NP on ELF levels of Alpha1-PI, ANEC, and Alpha1-PI: human neutrophil elastase (HNE) complexes in subjects with severe, congenital Alpha1-PI deficiency. A total of 13 subjects completed 8 weekly infusions of ARALAST NP at a median dose of 63 (range: 58 to 67) mg/kg body weight at an infusion rate of 0.2 mL/kg/min. Of the 13 subjects, 12 had both baseline and post-treatment bronchoalveolar lavage samples. ARALAST NP augmentation therapy resulted in a significant increase (p<0.0001; n=12) in the mean plasma of antigenic Alpha1-PI levels, from a median baseline level of 4.0 (range: 3.1 to 6.3) microM to a median post-treatment level of 14.6 (range: 11.1 to 18.1) microM. Post-treatment values of plasma Alpha1-PI were above 11 microM in all 12 subjects. Median plasma functional Alpha1-PI (ANEC) levels also increased significantly (p<0.0001; n=12) from a median baseline level of 2.5 (range: 1.6 to 3.0) microM to a median post-treatment level of 11.4 (range: 7.8 to 16.9) microM. While antigenic Alpha1-PI levels in the ELF also increased significantly (p=0.0195; n=10) (Figure 3), only 4 out of 12 subjects were observed to have measurable ELF ANEC level in either or both lung lobes following 8 weekly infusions of ARALAST NP and the difference from baseline among these subjects did not reach statistical significance. Changes in the ELF analytes free and total human neutrophil elastase, Alpha1-PI:HNE complexes, IL-8, and TNF alpha were either not statistically significant, or could not be analyzed due to limited data.

Changes in ELF Alpha1-PI (AAT) Levels Following Intravenous Treatment with ARALAST NP (60 mg/kg/week) for 8 Weeks in Subjects with Severe Congenital Alpha1-PI Deficiency

Figure 3

The clinical efficacy of ARALAST NP or any Alpha1-PI product in influencing the clinical course of pulmonary emphysema in Alpha1-PI deficiency has not been conclusively demonstrated in adequately powered, randomized, controlled clinical trials.

15 REFERENCES

1. Brantly M, Nukiwa T, Crystal RG. Molecular basis of alpha-1-antitrypsin deficiency. Am J Med 1988 (Suppl 6A); 84:13–31.
2. Crystal RG, Brantly ML, Hubbard RC, Curiel DT, et al. The alpha1-antitrypsin gene and its mutations: Clinical consequences and strategies for therapy. Chest 1989; 95:196–208.
3. Crystal RG. α1-Antitrypsin deficiency: pathogenesis and treatment. Hospital Practice 1991; Feb.15:81–94.
4. Hutchison DCS. Natural history of alpha-1-protease inhibitor deficiency. Am J Med 1988; 84(Suppl 6A):3–12.
5. Hubbard RC, Crystal RG. Alpha-1-antitrypsin augmentation therapy for alpha-1- antitrypsin deficiency. Am J Med 1988; 84(Suppl 6A):52–62.
6. Buist SA, Burrows B, Cohen A, et al. Guidelines for the approach to the patient with severe hereditary alpha-1-antitrypsin deficiency. Am Rev Respir Dis 1989; 140:1494–1497.
7. Gadek JE, Fells GA, Zimmerman RL, et al. Antielastases of the human alveolar structures: Implications for the protease-antiprotease theory of emphysema. J Clin Invest 1981; 68:889–898.
8. Kolarich D, et al. Biochemical, molecular characterization, and glycoproteomic analyses of α1-proteinase inhibitor products used for replacement therapy. Transfusion 2006; 46:1959–1977.
9. Transcript of Blood Products Advisory Committee (BPAC) 85th Meeting; 3-4 Nov 2005.
10. Turino GM, Barker AF, Brantly ML, et al: Clinical features of individuals with Pi*SZ phenotype of α1-antitrypsin deficiency. Am J Respir Crit Care Med 154: 1718–25, 1996.

16 HOW SUPPLIED/STORAGE AND HANDLING

How Supplied

ARALAST NP is available in the following kits:

Fill Size | Carton NDC
0.5 gram | 0944-2814-01
1 gram | 0944-2815-01

Each kit contains a suitable volume of Sterile Water for Injection, USP diluent (25 mL for 0.5 gram vial; 50 mL for 1 gram vial), one sterile double-ended transfer needle, one sterile 20 micron filter needle and one package insert.

Storage and Handling

- Store ARALAST NP at temperatures not to exceed 25°C (77°F).
- Do not freeze.
- Do not use after the expiration date printed on the label.
- Store ARALAST NP in the original carton to protect from light.

17 PATIENT COUNSELING INFORMATION

- Inform patients of the early signs of hypersensitivity reactions, including hives, generalized urticaria, chest tightness, dyspnea, wheezing, faintness, hypotension, and anaphylaxis. Advise patients to discontinue use of the product and contact their physician and/or seek immediate emergency care, depending on the severity of the reaction, if these symptoms occur.
- Inform patients that ARALAST NP is made from human plasma, therefore the possibility of transmitting infectious agents cannot be totally excluded. Explain that the risk of transmitting an infectious agent has been reduced by screening donors, testing plasma for certain virus infections, and a manufacturing process to inactivate and/or remove certain viruses.
- Inform patients that administration of ARALAST NP has been demonstrated to raise the levels of Alpha1-PI in the blood and in the lung, but that the effect of this augmentation on the frequency of pulmonary exacerbations and on the rate of progression of emphysema has not been established by clinical trials.

Takeda Pharmaceuticals U.S.A., Inc.
Cambridge, MA 02142
U.S. License No. 1898

ARALAST is a registered trademark of Baxalta Incorporated.
Takeda and are registered trademarks of Takeda Pharmaceutical Company Limited.
PROLASTIN® is a registered trademark of Grifols Therapeutics LLC.

©2025 Takeda Pharmaceutical Company Limited. All rights reserved.

PRINCIPAL DISPLAY PANEL - Kit Carton - 0.5 gram

NDC 0944-2814-01
0.5 gram

Alpha1-Proteinase
Inhibitor (Human)
Aralast® NP

Solvent Detergent Treated
Nanofiltered

Lyophilized powder for solution

For intravenous use only

Rx only

Takeda

PRINCIPAL DISPLAY PANEL - 0.5 gram Vial Label

NDC 0944-2803-03
0.5 gram

Alpha1-Proteinase
Inhibitor (Human)
Aralast®NP

Solvent Detergent Treated
Nanofiltered

Lyophilized powder for solution
ARALAST is a registered trademark of
Baxalta Incorporated.

Rx only

Takeda

PRINCIPAL DISPLAY PANEL - Kit Carton - 1 gram

NDC 0944-2815-01
1 gram

Alpha1-Proteinase
Inhibitor (Human)
Aralast® NP

Solvent Detergent Treated
Nanofiltered

Lyophilized powder for solution

For intravenous use only

Rx only

Takeda

PRINCIPAL DISPLAY PANEL - 1 gram Vial Label

NDC 0944-2804-04
1 gram

Alpha1-Proteinase
Inhibitor (Human)
Aralast® NP

Solvent Detergent Treated
Nanofiltered

Lyophilized powder for solution
ARALAST is a registered trademark of Baxalta
Incorporated.

Rx only

Takeda